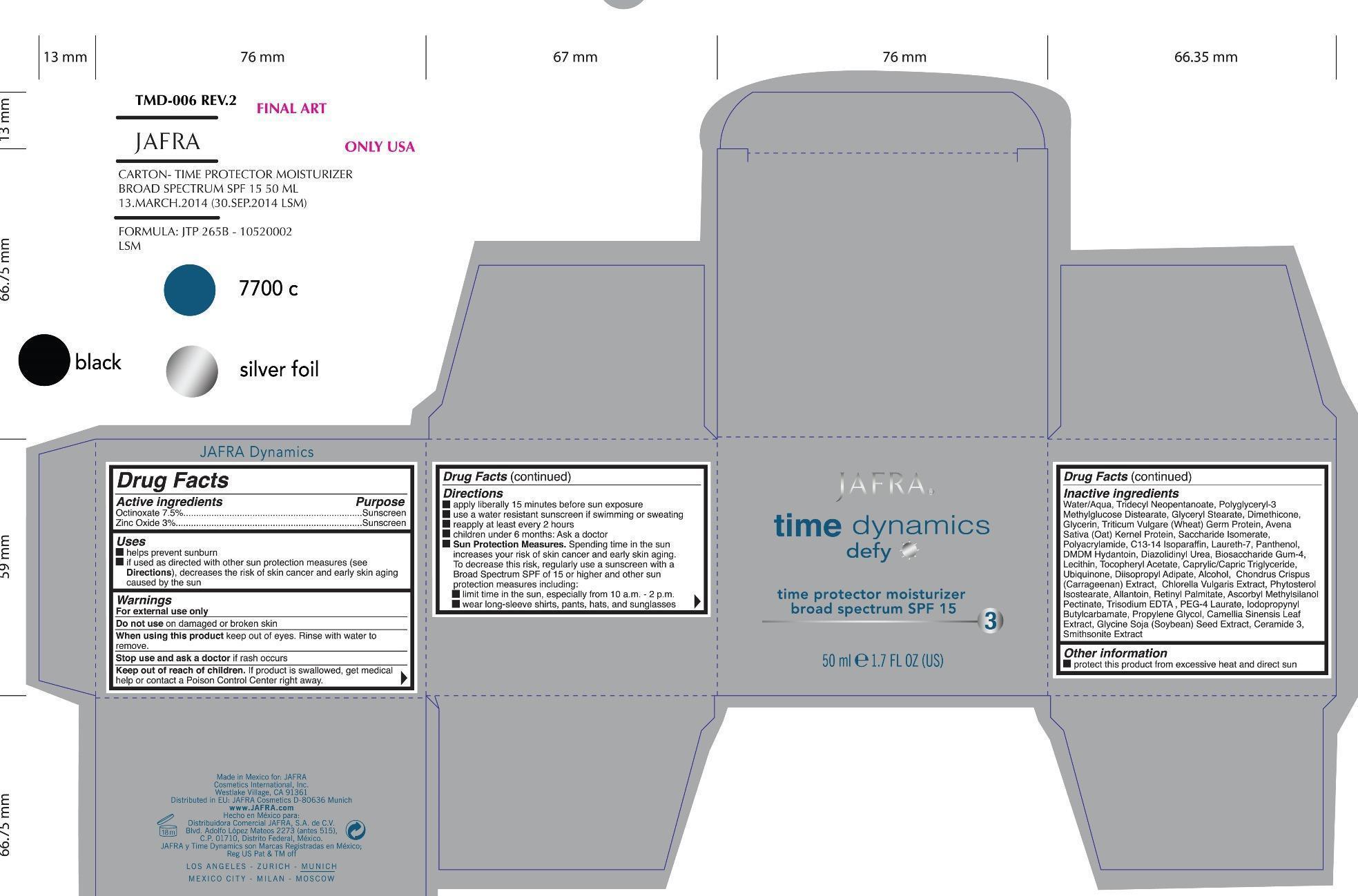 DRUG LABEL: defy time protector moisturizer broad spectrum SPF 15
NDC: 68828-201 | Form: CREAM
Manufacturer: Jafra Cosmetics International
Category: otc | Type: HUMAN OTC DRUG LABEL
Date: 20190521

ACTIVE INGREDIENTS: OCTINOXATE 7.5 g/100 mL; ZINC OXIDE 3 g/100 mL
INACTIVE INGREDIENTS: WATER; TRIDECYL NEOPENTANOATE; GLYCERYL MONOSTEARATE; DIMETHICONE; GLYCERIN; WHEAT GERM; SACCHARIDE ISOMERATE; POLYACRYLAMIDE (1500 MW); C13-14 ISOPARAFFIN; LAURETH-7; PANTHENOL; DMDM HYDANTOIN; DIAZOLIDINYL UREA; BIOSACCHARIDE GUM-4; LECITHIN, SOYBEAN; .ALPHA.-TOCOPHEROL ACETATE; MEDIUM-CHAIN TRIGLYCERIDES; UBIDECARENONE; DIISOPROPYL ADIPATE; ALCOHOL; CHONDRUS CRISPUS CARRAGEENAN; CHLORELLA VULGARIS; ALLANTOIN; VITAMIN A PALMITATE; ASCORBYL METHYLSILANOL PECTINATE; EDETATE TRISODIUM; PEG-4 LAURATE; IODOPROPYNYL BUTYLCARBAMATE; PROPYLENE GLYCOL; GREEN TEA LEAF; SOYBEAN; CERAMIDE 3

Active Ingredients Purpose

Octinoxate 7.5% Sunscreen

Zinc Oxide 3% Sunscreen

Uses

- helps prevent sunburn
- if used as directed with other sun protection measures (see Directions), decreases the risk of skin cancer and early skin aging caused by the sun

Keep out of reach of children. If product is swallowed, get medical help or contact a Poison Contol Center right away.

Stop use and ask a doctor if rash occurs

Warnings

- For external use only
- Do not use on damaged or broken skin
- When using this product keep out of eyes. Rinse with water to remove.

Directions

- apply liberally 15 minutes before sun exposure
- use a water resistant sunscreen if swimming or sweating
- reapply at least every 2 hours
- children under 6 months: Ask a doctor
- Sun Protection Measures. Spending time in the sun increases your risk of skin cancer and early skin aging. To decrease this risk, regularly use a sunscreen with a Broad Spectrum of SPF 15 or higher and other sun protection measures including:

limit time in the sun, especially from 10a.m - 2p.m.

wear long-sleeve shirts, pants, hats, and sunglasses

Inactive Ingredients

Water/Aqua, Tridecyl Neopentanoate, Polyglyceryl-3 Methylglucose Distearate, Glyceryl Stearate, Dimethicone, Glycerin, Triticum Vulgare (Wheat) Germ Protein, Avena Sativa (Oat) Kernel Protein,Saccharide lsomerate, Polyacrylamide, C13-141soparaffin, Laureth-7, Panthenol, DMDM Hydantoin, Diazolidinyl Urea, Biosaccharide Gum-4, Lecithin,Tocopheryl Acetate, Caprylic/Capric Triglylceride, Ubiquinone, Diisopropyl Adipate, Alcohol, Chondrus Crispus (Carrageenan) Extract, Chlorella Vulgaris Extract, Phytosterol lsostearate, Allantoin, Retinyl Palmitate, Ascorbyl Methylsilanol Pectinate, Trisodium EDTA, PEG-4 Laurate, lodopropynyl Bulylcarbamate, Propylene Glycol, Camellia Sinensis Leal Extract, Glycine Soja (Soybean) Seed Extract, Ceramide 3, Smithsonite Extract

PACKAGE LABEL

Jafra

time dynamics defy

Time protector Moisturizer broad spectrum SPF 15

50ml 1.7fl oz